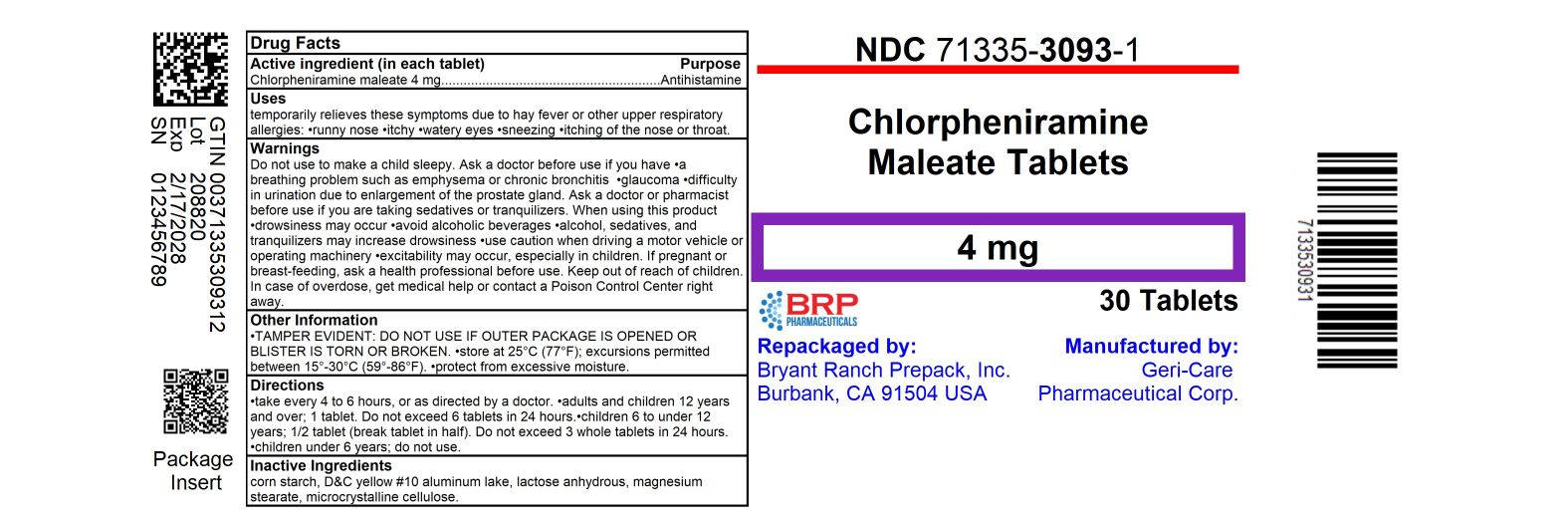 DRUG LABEL: Allergy Relief
NDC: 71335-3093 | Form: TABLET
Manufacturer: Bryant Ranch Prepack
Category: otc | Type: HUMAN OTC DRUG LABEL
Date: 20260217

ACTIVE INGREDIENTS: CHLORPHENIRAMINE MALEATE 4 mg/1 1
INACTIVE INGREDIENTS: STARCH, CORN; D&C YELLOW NO. 10; MAGNESIUM STEARATE; MICROCRYSTALLINE CELLULOSE; ANHYDROUS LACTOSE

HST 784 (974)

Active ingredient (in each tablet)

Chlorpheniramine maleate 4 mg

Purpose

Antihistamine

Uses

temporarily relieves these symptoms due to hay fever or other upper respiratory allergies:

- runny nose
- itchy, watery eyes
- sneezing
- itching of the nose or throat

Warnings

Do not use

to make a child sleepy.

Ask a doctor before use if you have

- glaucoma
- a breathing problem such as emphysema or chronic bronchitis
- trouble urinating due to an enlarged prostate gland

Ask a doctor or pharmacist before use if you are

taking sedatives or tranquilizers.

When using this product

- drowsiness may occur
- avoid alcoholic beverages
- alcohol, sedatives, and tranquilizers may increase drowsiness
- use caution when driving a motor vehicle or operating machinery
- excitability may occur, especially in children

If pregnant or breast-feeding,

ask a health professional before use.

Keep out of reach of children.

In case of overdose, get medical help or contact a Poison Control Center right away.

Directions

• do not exceed recommended dose
• adults and children 12 years and over: take 1 tablet every 4 to 6 hours,
as needed, not more than 6 tablets in 24 hours or as directed by a doctor
• children under 12: consult a doctor

Other information

• Tamper Evident: Do not use if imprinted seal
under cap is missing or broken. • store at 20-25°C (68-77°F);
excursions permitted between 15°-30°C (59°-86°F)
• protect from moisture

Inactive ingredients

corn starch, D&C yellow #10 aluminum lake, lactose anhydrous, magnesium stearate, microcrystalline cellulose

Questions or comments?

1-800-540-3765

HOW SUPPLIED

Chlorpheniramine Maleate 4mg Tablets

- NDC 71335-3093-1: 30 Tablets in a BOTTLE
- NDC 71335-3093-2: 60 Tablets in a BOTTLE
- NDC 71335-3093-3: 100 Tablets in a BOTTLE
- NDC 71335-3093-4: 120 Tablets in a BOTTLE
- NDC 71335-3093-5: 40 Tablets in a BOTTLE
- NDC 71335-3093-6: 24 Tablets in a BOTTLE

Repackaged/Relabeled by:
Bryant Ranch Prepack
Burbank, CA 91504

PACKAGE LABEL

Chlorpheniramine Maleate 4mg Tablets